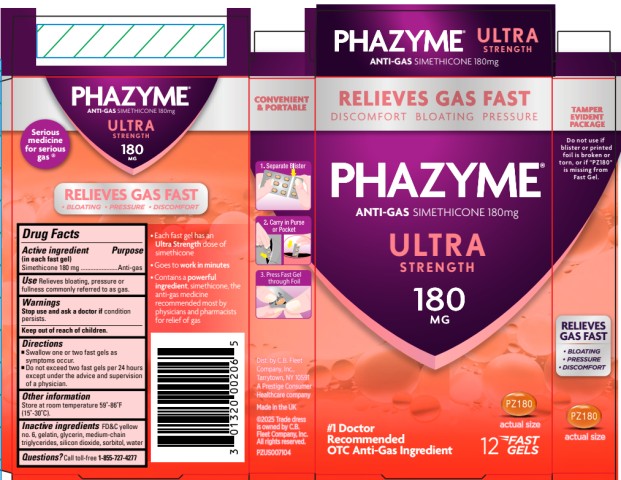 DRUG LABEL: PHAZYME
NDC: 0132-0208 | Form: CAPSULE, GELATIN COATED
Manufacturer: C.B. Fleet Company, Inc.
Category: otc | Type: HUMAN OTC DRUG LABEL
Date: 20251023

ACTIVE INGREDIENTS: DIMETHICONE 180 mg/1 1
INACTIVE INGREDIENTS: FD&C YELLOW NO. 6; GELATIN; GLYCERIN; MEDIUM-CHAIN TRIGLYCERIDES; SILICON DIOXIDE; SORBITOL; WATER

Phazyme Ultra Strength 180 mg 0132-0208

PHAZYME- SIMETHICONE CAPSULE, GELATIN COATED

Phazyme Ultra Strength 180 mg 0132-0208

Drug Facts

Active Ingredient (in each fast gel)

Simethicone 180mg

Purpose

Anti-gas

Use

Relieves bloating, pressure or fullness commonly referred to as gas

Warnings

Stop use and ask a doctor if

condition persists.

Directions

- Swallow one or two fast gels as symptoms occur
- Do not exceed two fast gels per 24 hours except under the advice and supervision of a physician

Other information

Store at room temperature 59°-86°F (15°-30°C).

Inactive Ingredients

FD&C yellow no. 6, gelatin, glycerin, medium-chain triglycerides, silicon dioxide, sorbitol, water

Questions?

Call toll-free 1-855-727-4277

TAMPER EVIDENT PACKAGE

Do not use if blister or printed foil is broken or torn, or if “PZ180” is missing from Fast Gel.

Principal Display Panel

PHAZYME® ULTRA STRENGTH

ANTI-GAS SIMETHICONE 180 MG

12 fast gels